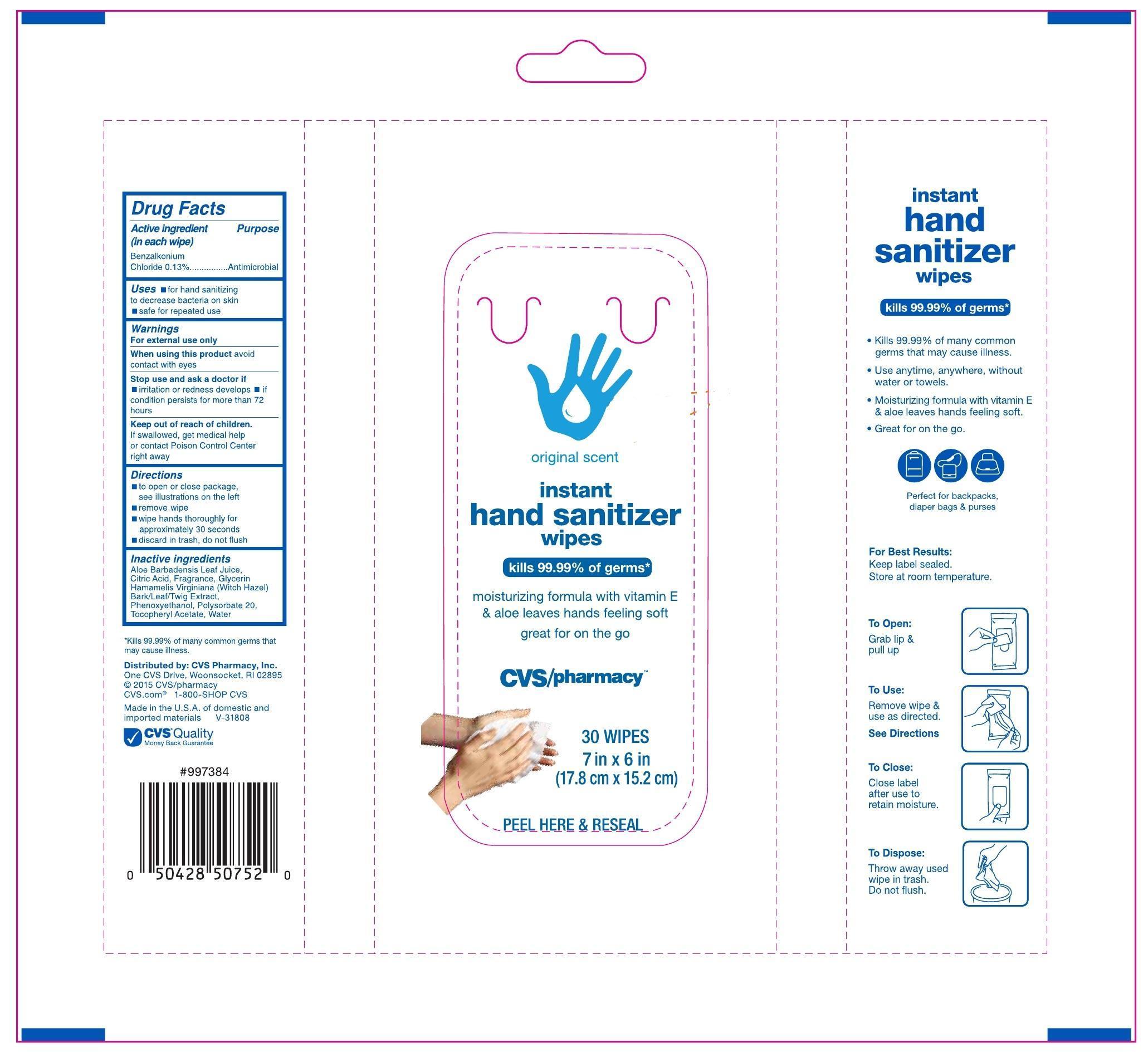 DRUG LABEL: Instant Hand Sanitizer Wipes
NDC: 59779-665 | Form: CLOTH
Manufacturer: CVS
Category: otc | Type: HUMAN OTC DRUG LABEL
Date: 20150930

ACTIVE INGREDIENTS: BENZALKONIUM CHLORIDE .13 mg/100 mL; .ALPHA.-TOCOPHEROL ACETATE, DL- 1 mg/100 mL
INACTIVE INGREDIENTS: ALOE VERA LEAF 1 mg/100 mL; CITRIC ACID ACETATE 1 mg/100 mL; GLYCERIN 1 mg/100 mL; HAMAMELIS VIRGINIANA ROOT BARK/STEM BARK 1 mg/100 mL; PHENOXYETHANOL 1 mg/100 mL; POLYSORBATE 20 1 mg/100 mL; WATER 1 mL/100 mL

Inactive ingredients

Aloe Barbadensis Leaf Juice, Citric Acid, Fragrance, Glycerin, Hamamelis Virginiana (Witch Hazel) Bark/Leaf/Twig Extract, Phenoxyethanol, Polysorbate 20, Tocopheryl Acetate, Water

Active Ingredient

Benzalkonium Chloride 0.13%

Purpose

Antimicrobial

Directions

- To open or close package see illustrations on the left
- remove wipe
- wipe hands thoroughly for 30 seconds
- discard in trash, do not flush

Warnings

For External Use Only

When using this product avoid contact with eyes,

Stop use and ask a doctor

- if irritation or redness develop
- if conditions persists for more than 72 hours

Keep out of reach of children

If swallowed, get medical help or contact Poision Control Center right away.